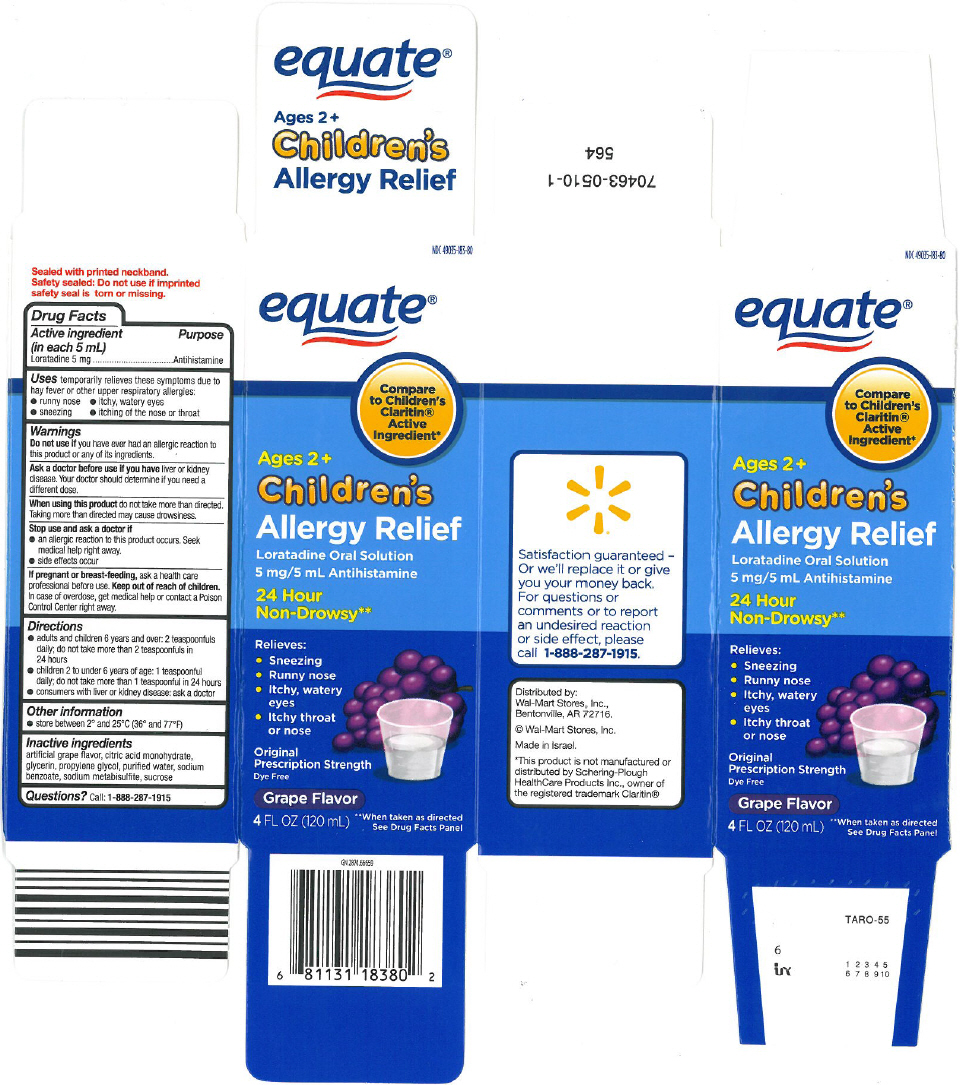 DRUG LABEL: Childrens allergy relief
NDC: 49035-183 | Form: SOLUTION
Manufacturer: Wal-Mart Stores Inc
Category: otc | Type: HUMAN OTC DRUG LABEL
Date: 20121024

ACTIVE INGREDIENTS: Loratadine 5 mg/5 mL
INACTIVE INGREDIENTS: citric acid monohydrate; glycerin; propylene glycol; water; sodium benzoate; sodium metabisulfite; sucrose

Children's allergy relief

Drug Facts

Active ingredient (in each 5 mL)

Loratadine 5 mg

Purpose

Antihistamine

Uses

temporarily relieves these symptoms due to hay fever or other upper respiratory allergies:

- runny nose
- itchy, watery eyes
- sneezing
- itching of the nose or throat

Warnings

Do not use if you have ever had an allergic reaction to this product or any of its ingredients.

Ask a doctor before use if you have liver or kidney disease. Your doctor should determine if you need a different dose.

When using this product do not take more than directed. Taking more than directed may cause drowsiness.

Stop use and ask a doctor if

- an allergic reaction to this product occurs. Seek medical help right away.
- side effects occur.

PREGNANCY OR BREAST FEEDING

If pregnant or breast-feeding, ask a health care professional before use.

Keep out of reach of children. In case of overdose, get medical help or contact a Poison Control Center right away.

Directions

- adults and children 6 years and over: 2 teaspoonfuls daily; do not take more than 2 teaspoonfuls in 24 hours
- children 2 to under 6 years of age: 1 teaspoonful daily; do not take more than 1 teaspoonful in 24 hours
- consumers with liver or kidney disease: ask a doctor

Other information

- store between 2° and 25°C (36° and 77°F)

Inactive ingredients

artificial grape flavor, citric acid monohydrate, glycerin, propylene glycol, purified water, sodium benzoate, sodium metabisulfite, sucrose

Questions?

Call: 1-888-287-1915

Distributed by:
Wal-Mart Stores, Inc.,
Bentonville, AR 72716.

PRINCIPAL DISPLAY PANEL - 120 mL Bottle Carton

NDC 49035-183-80

equate®

Compare
to Children's
Claritin®
Active
Ingredient*

Ages 2+
Children's
Allergy Relief
Loratadine Oral Solution
5 mg/5 mL Antihistamine

24 Hour
Non-Drowsy**

Relieves:

- Sneezing
- Runny nose
- Itchy, watery
  eyes
- Itchy throat
  or nose

Original
Prescription Strength
Dye Free

Grape Flavor

4 FL OZ (120 mL)

**When taken as directed
See Drug Facts Panel